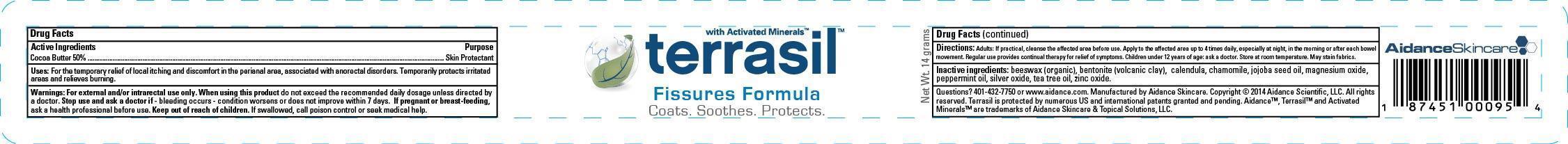 DRUG LABEL: Terrasil Fissures Formula
NDC: 24909-118 | Form: OINTMENT
Manufacturer: Aidance Skincare & Topical Solutions, LLC
Category: otc | Type: HUMAN OTC DRUG LABEL
Date: 20140610

ACTIVE INGREDIENTS: COCOA BUTTER 50 g/100 g
INACTIVE INGREDIENTS: BENTONITE; CALENDULA OFFICINALIS FLOWER; CHAMOMILE; JOJOBA OIL; MAGNESIUM OXIDE; PEPPERMINT OIL; SILVER OXIDE; TEA TREE OIL; WHITE WAX; ZINC OXIDE

Drug Facts

Active Ingredient

Cocoa Butter 50%

Purpose

Skin Protectant

Uses

For the temporary relief of local itching and discomfort in the perianal area, associated with anorectal disorders. Temporarily forms a protective coating over inflamed tissues to help prevent drying of tissues. Temporarily protects irritated areas. Temporarily relieves burning.

Warnings

For external and/or intrarectal use only. When using this product do not exceed the recommended daily dosage unless directed by a doctor. Stop use and ask a doctor if - bleeding occurs - condition worsens or does not improve within 7 days. If pregnant or breast-feeding, ask a health professional before use.

Keep out of reach of children.

If swallowed, get medical help or call a Poison Control Center right away.

Directions

Adults: If practical, cleanse the affected area before use. Apply to the affected area up to 4 times daily, especially at night, in the morning or after each bowel movement. Regular use provides continual therapy for relief of symptoms. Children under 12 years of age: ask a doctor.

Inactive Ingredients

beeswax (organic), bentonite (volcanic clay), calendula, chamomile, jojoba seed oil, magnesium oxide, peppermint oil, silver oxide, tea tree oil, zinc oxide.

PRINCIPAL DISPLAY PANEL - 14g Label

terrasil with Activated Minerals

Fissures Formula
Coats. Soothes. Protects.